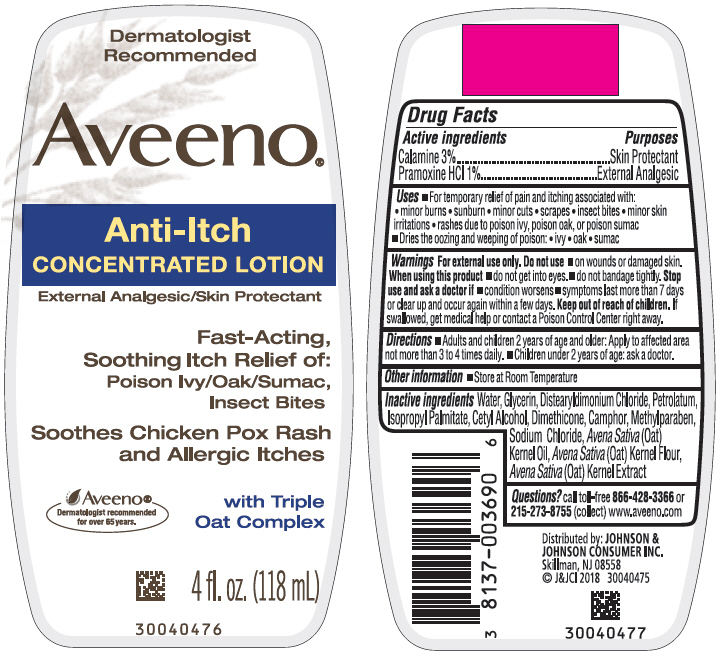 DRUG LABEL: Aveeno Anti-Itch Concentrated
NDC: 69968-0475 | Form: LOTION
Manufacturer: Kenvue Brands LLC
Category: otc | Type: HUMAN OTC DRUG LABEL
Date: 20251029

ACTIVE INGREDIENTS: ZINC OXIDE 29.4 mg/1 mL; FERRIC OXIDE RED 0.6 mg/1 mL; PRAMOXINE HYDROCHLORIDE 10 mg/1 mL
INACTIVE INGREDIENTS: WATER; GLYCERIN; DISTEARYLDIMONIUM CHLORIDE; PETROLATUM; ISOPROPYL PALMITATE; CETYL ALCOHOL; DIMETHICONE; METHYLPARABEN; SODIUM CHLORIDE; OAT KERNEL OIL; OATMEAL; OAT

Aveeno® Anti-Itch CONCENTRATED LOTION

Drug Facts

ACTIVE INGREDIENT

Active ingredients | Purpose
Calamine 3% | Skin Protectant
Pramoxine HCl 1% | External Analgesic

Uses

- For temporary relief of pain and itching associated with:
  - minor burns
  - sunburn
  - minor cuts
  - scrapes
  - insect bites
  - minor skin irritations
  - rashes due to poison ivy, poison oak, or poison sumac
- Dries the oozing and weeping of poison:
  - ivy
  - oak
  - sumac

Warnings

For external use only.

Do not use

- on wounds or damaged skin

When using this product

- do not get into eyes
- do not bandage tightly

Stop use and ask a doctor if

- condition worsens
- symptoms last more than 7 days or clear up and occur again within a few days

Keep out of reach of children. If swallowed, get medical help or contact a Poison Control Center right away.

Directions

- Adults and children 2 years of age and older: Apply to affected area not more than 3 to 4 times daily.
- Children under 2 years of age: ask a doctor.

Other information

- Store at Room Temperature

Inactive ingredients

Water, Glycerin, Distearyldimonium Chloride, Petrolatum, Isopropyl Palmitate, Cetyl Alcohol, Dimethicone, Camphor, Methylparaben, Sodium Chloride, Avena Sativa (Oat) Kernel Oil, Avena Sativa (Oat) Kernal Flour, Avena Sativa (Oat) Kernel Extract

Questions?

call toll-free 866-428-3366 or 215-273-8755(collect) www.aveeno.com

Distributed by: JOHNSON &
JOHNSON CONSUMER INC.
Skillman, NJ 08558

PRINCIPAL DISPLAY PANEL - 118 mL Bottle Label

Dermatologist
Recommended

Aveeno®

Anti-Itch
CONCENTRATED LOTION
External Analgesic/Skin Protectant

Fast-Acting,
Soothing Itch Relief of:
Poison Ivy/Oak/Sumac,
Insect Bites

Soothes Chicken Pox Rash
and Allergic Itches

Aveeno®
Dermatologist recommended
for over 65 years

with Triple
Oat Complex

4 fl. oz. (118 mL)